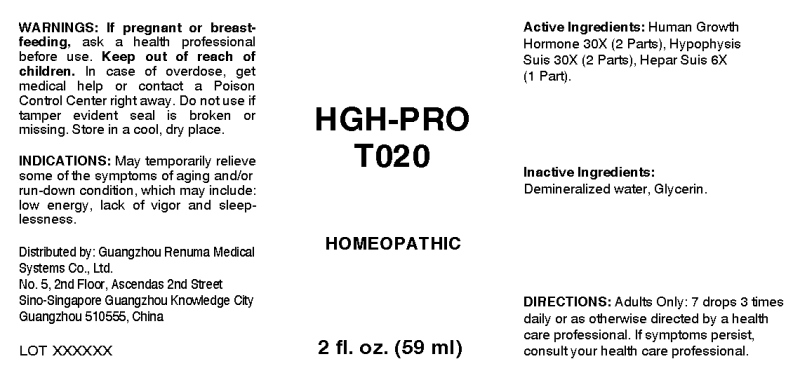 DRUG LABEL: HGH-Pro
NDC: 71742-0014 | Form: LIQUID
Manufacturer: Guangzhou Renuma Medical Systems Co., Ltd
Category: homeopathic | Type: HUMAN OTC DRUG LABEL
Date: 20171031

ACTIVE INGREDIENTS: SOMATROPIN 30 [hp_X]/1 mL; SUS SCROFA PITUITARY GLAND 30 [hp_X]/1 mL; PORK LIVER 6 [hp_X]/1 mL
INACTIVE INGREDIENTS: WATER; GLYCERIN

Drug Facts:

ACTIVE INGREDIENTS:

Human Growth Hormone 30X (2 Parts), Hypophysis Suis 30X (2 Parts), Hepar Suis 6X (1 Part).

USES:

May temporarily relieve some of the symptoms of aging and/or run-down condition, which may include: low energy, lack of vigor and sleeplessness.

WARNINGS:

If pregnant or breast-feeding, ask a health care professional before use.
Keep out of reach of children. In case of overdose, get medical help or contact a Poison Control Center right away.
Do not use if tamper evident seal is broken or missing.
Store in cool, dry place.

Keep out of reach of children. In case of overdose, get medical help or contact a Poison Control Center right away.

DIRECTIONS:

Adults only: 7 drops 3 times daily or as otherwise directed by a health care professional. If symptoms persist, consult your health care professional.

USES:

May temporarily relieve some of the symptoms of aging and/or run-down condition, which may include: low energy, lack of vigor and sleeplessness.

INACTIVE INGREDIENTS:

Demineralized water, Glycerin.

QUESTIONS:

Distributed by:
Guangzhou Renuma Medical
Systems Co., Ltd.
No. 5, 2nd Floor, Ascendas 2nd Street
Sino-Singapore Guangzhou Knowledge City
Guangzhou 510555, China

PACKAGE LABEL DISPLAY:

HGH-PRO
T020
HOMEOPATHIC
2 fl. oz. (59 ml)